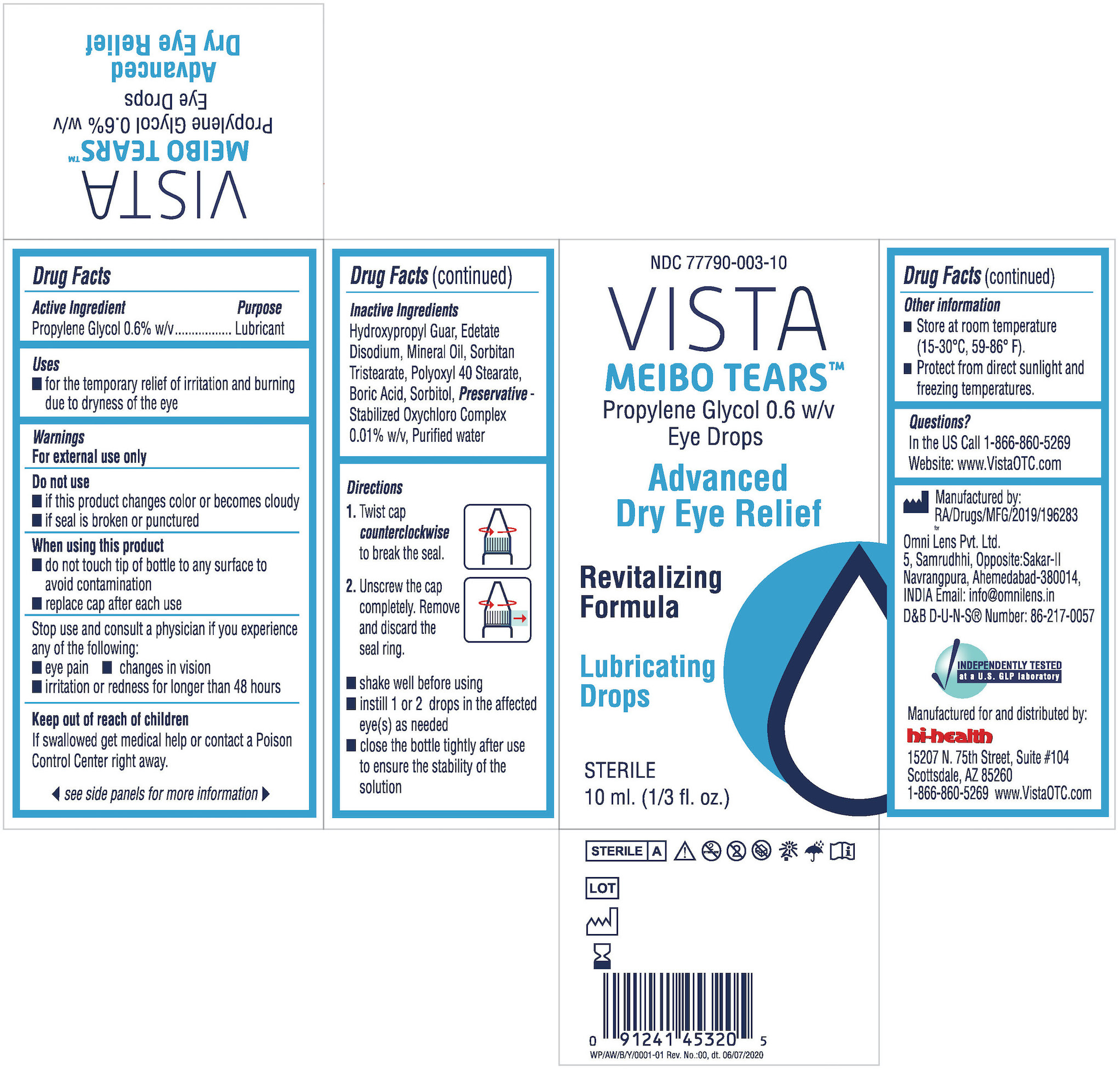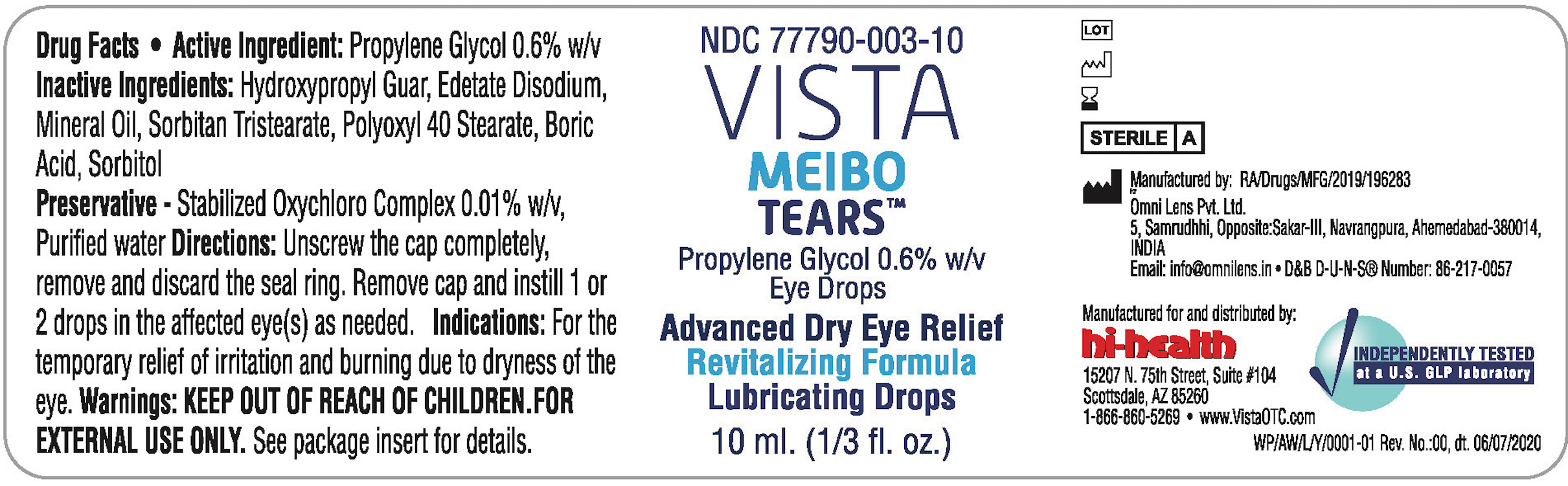 DRUG LABEL: VISTA MEIBO TEARS Propylene Glycol 0.6% w/v Advanced Dry Eye Relief Lubricating Drops 10 ml
NDC: 77790-003 | Form: LIQUID
Manufacturer: Red Wedding LLC
Category: otc | Type: HUMAN OTC DRUG LABEL
Date: 20250101

ACTIVE INGREDIENTS: PROPYLENE GLYCOL 0.6 g/100 mL
INACTIVE INGREDIENTS: WATER; MINERAL OIL; SORBITAN TRISTEARATE; POLYOXYL 40 STEARATE; BORIC ACID; EDETATE DISODIUM; GUARAPROLOSE (1300 MPA.S AT 1%)

Vista Meibo Tears Propylene Glycol 0.6% w/v Advanced Dry Eye Relief Revitalizing Formula Lubricating Drops

Active ingredient

Propylene glycol 0.6%

Purpose

Lubricant

Uses

- For the temporary relief of irritation and burning due to dryness of the eye

Warnings

For external use only.

Do not use

- if this product changes color or becomes cloudy
- if seal is broken or punctured

When using this product

- do not touch tip of bottle to any surface to avoid contamination
- replace cap after each use

Stop use and consult a physician if you experience any of the following:

- eye pain
- changes in vision
- irritation or redness for longer than 48 hours

Keep out of reach of children.

- If swallowed, get medical help or contact a Poison Control Center right away.

Directions

- shake well before using.
- instill 1 or 2 drops in the affected eye(s) as needed.

Other information

- Store at room temperature (15-30^0C, 59-86^0F).
- Protect from direct sunlight and freezing temperatures.

Inactive ingredients

Hydroxypropyl Guar, Edetate Disodium, Mineral Oil, Sorbitan Tristearate, Polyoxyl 40 Stearate, Boric Acid, Sorbitol

Preservative - Stabilized Oxychloro Complex 0.01% w/v, Purified water